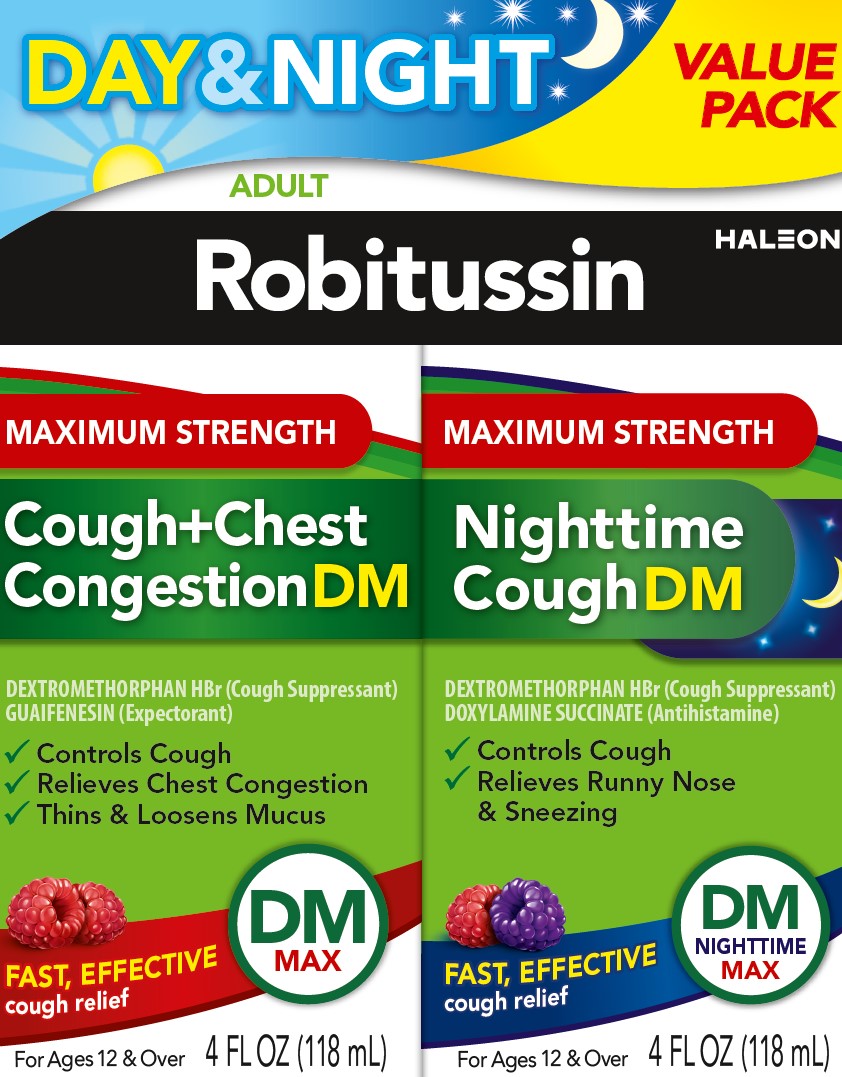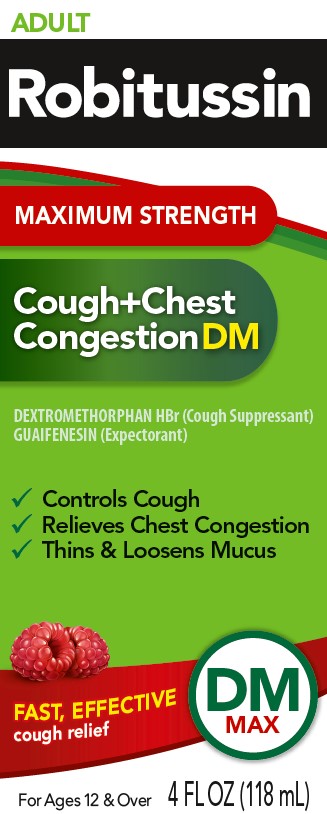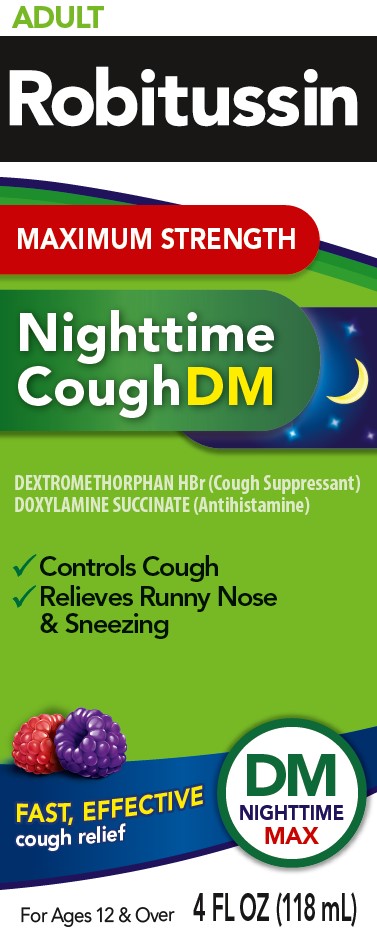 DRUG LABEL: Robitussin

NDC: 0031-2103 | Form: KIT | Route: ORAL
Manufacturer: Haleon US Holdings LLC
Category: otc | Type: HUMAN OTC DRUG LABEL
Date: 20251107

ACTIVE INGREDIENTS: DEXTROMETHORPHAN HYDROBROMIDE 20 mg/20 mL; GUAIFENESIN 400 mg/20 mL; DEXTROMETHORPHAN HYDROBROMIDE 30 mg/20 mL; DOXYLAMINE SUCCINATE 12.5 mg/20 mL
INACTIVE INGREDIENTS: ANHYDROUS CITRIC ACID; CARBOXYMETHYLCELLULOSE SODIUM, UNSPECIFIED; FD&C BLUE NO. 1; FD&C RED NO. 40; GLYCERIN; DEXTROSE, UNSPECIFIED FORM; MENTHOL, UNSPECIFIED FORM; POLYETHYLENE GLYCOL, UNSPECIFIED; PROPYLENE GLYCOL; WATER; SODIUM BENZOATE; SODIUM CITRATE, UNSPECIFIED FORM; SUCRALOSE; TRIACETIN; XANTHAN GUM; ANHYDROUS CITRIC ACID; CARBOXYMETHYLCELLULOSE SODIUM, UNSPECIFIED; FD&C BLUE NO. 1; FD&C RED NO. 40; GLYCERIN; DEXTROSE, UNSPECIFIED FORM; MENTHOL, UNSPECIFIED FORM; POLYETHYLENE GLYCOL, UNSPECIFIED; PROPYLENE GLYCOL; WATER; SODIUM BENZOATE; SODIUM CITRATE, UNSPECIFIED FORM; SUCRALOSE; TRIACETIN; XANTHAN GUM

Drug Facts

Active ingredients (in each 20 mL)– Robitussin Maximum Strength Cough+Chest Congestion DM

Dextromethorphan HBr, USP 20 mg

Guaifenesin, USP 400 mg

Purposes– Robitussin Maximum Strength Cough+Chest Congestion DM

Cough suppressant

Expectorant

Uses– Robitussin Maximum Strength Cough+Chest Congestion DM

- temporarily relieves cough due to minor throat and bronchial irritation as may occur with a cold
- helps loosen phlegm (mucus) and thin bronchial secretions to drain bronchial tubes

Warnings– Robitussin Maximum Strength Cough+Chest Congestion DM

Do not use

if you are now taking a prescription monoamine oxidase inhibitor (MAOI) (certain drugs for depression, psychiatric, or emotional conditions, or Parkinson's disease), or for 2 weeks after stopping the MAOI drug. If you do not know if your prescription drug contains an MAOI, ask a doctor or pharmacist before taking this product.

Ask a doctor before use if you have

- cough that occurs with too much phlegm (mucus)
- cough that lasts or is chronic such as occurs with smoking, asthma, chronic bronchitis, or emphysema

Stop use and ask a doctor if

cough lasts more than 7 days, comes back, or is accompanied by fever, rash, or persistent headache.

These could be signs of a serious condition.

If pregnant or breast-feeding,

ask a health professional before use.

Keep out of reach of children.

In case of overdose, get medical help or contact a Poison Control Center right away.

Directions– Robitussin Maximum Strength Cough+Chest Congestion DM

- do not take more than 6 doses in any 24 hour period
- measure only with dosing cup provided
- keep dosing cup with product
- mL = milliliter
- this adult product is not intended for use in children under 12 years of age

age | dose
adults and children 12 years and over | 20 mL every 4 hours
children under 12 years | do not use

Other information– Robitussin Maximum Strength Cough+Chest Congestion DM

- each 20 mL contains:sodium 13 mg
- store at 20-25°C (68-77°F). Do not refrigerate.

Inactive ingredients– Robitussin Maximum Strength Cough+Chest Congestion DM

anhydrous citric acid, carboxymethylcellulose sodium, FD&C blue no. 1, FD&C red no. 40, glycerin, liquid glucose, menthol, natural and artificial flavors, polyethylene glycol, propylene glycol, purified water, sodium benzoate, sodium citrate, sucralose, triacetin, xanthan gum

Questions or comments?– Robitussin Maximum Strength Cough+Chest Congestion DM

call weekdays from 8 AM to 6 PM EST at 1-800-245-1040

Active ingredients (in each 20 mL)– Robitussin Maximum Strength Nighttime Cough DM

Dextromethorphan HBr, USP 30 mg

Doxylamine succinate, USP 12.5 mg

Purposes– Robitussin Maximum Strength Nighttime Cough DM

Cough suppressant

Antihistamine

Uses– Robitussin Maximum Strength Nighttime Cough DM

- temporarily relieves cough due to minor throat and bronchial irritation as may occur with a cold
- temporarily relieves these symptoms due to hay fever or other upper respiratory allergies:
  - runny nose
  - sneezing
  - itchy, watery eyes
  - itching of the nose or throat
- controls the impulse to cough to help you sleep

Warnings– Robitussin Maximum Strength Nighttime Cough DM

Do not use

- to sedate a child or to make a child sleepy
- if you are now taking a prescription monoamine oxidase inhibitor (MAOI) (certain drugs for depression, psychiatric, or emotional conditions, or Parkinson's disease), or for 2 weeks after stopping the MAOI drug. If you do not know if your prescription drug contains an MAOI, ask a doctor or pharmacist before taking this product.

Ask a doctor before use if you have

- trouble urinating due to an enlarged prostate gland
- glaucoma
- a cough that occurs with too much phlegm (mucus)
- a breathing problem or chronic cough that lasts or as occurs with smoking, asthma, chronic bronchitis or emphysema

Ask a doctor or pharmacist before use if you are

taking sedatives or tranquilizers

When using this product

- do not use more than directed
- marked drowsiness may occur
- avoid alcoholic drinks
- alcohol, sedatives, and tranquilizers may increase drowsiness
- be careful when driving a motor vehicle or operating machinery
- excitability may occur, especially in children

Stop use and ask a doctor if

cough lasts more than 7 days, comes back, or is accompanied by a fever, rash, or persistent headache.

These could be signs of a serious condition.

If pregnant or breast-feeding,

ask a health professional before use.

Keep out of reach of children.

In case of overdose, get medical help or contact a Poison Control Center right away.

Directions– Robitussin Maximum Strength Nighttime Cough DM

- measure only with dosing cup provided
- keep dosing cup with product
- mL = milliliter
- do not take more than 4 doses in any 24-hour period
- this adult product is not intended for use in children under 12 years of age

age | dose
adults and children 12 years and over | 20 mL every 6 hours
children under 12 years | do not use

Other information– Robitussin Maximum Strength Nighttime Cough DM

- each 20 mL contains:sodium 14 mg
- store at 20-25°C (68-77°F)

Inactive ingredients– Robitussin Maximum Strength Nighttime Cough DM

anhydrous citric acid, carboxymethylcellulose sodium, FD&C blue no. 1, FD&C red no. 40, glycerin, liquid glucose, menthol, natural and artificial flavors, polyethylene glycol, propylene glycol, purified water, sodium benzoate, sodium citrate, sucralose, triacetin, xanthan gum

Questions or comments?– Robitussin Maximum Strength Nighttime Cough DM

call weekdays from 9 AM to 5 PM EST at 1-800-245-1040

Additional information– Robitussin Maximum Strength Day/Night Value Pack

TAMPER-EVIDENT INNER UNITS:

Do Not Use if Tamper-Evident feature on either bottle cap is broken or missing. See individual inner cartons and bottle labels for specific Tamper-Evident features.

Do not take both products within 6 hours of each other.

STRONG SOOTHING ACTION and fast, powerful cough relief

PARENTS: Learn about teen medicine abuse

www.StopMedicineAbuse.org

Principal Display Panel – Robitussin Maximum Strength Cough+Chest Congestion DM

ADULT

Robitussin

MAXIMUM STRENGTH

Cough+Chest Congestion DM

DEXTROMETHORPHAN HBr (Cough Suppressant)

GUAIFENESIN (Expectorant)

- Controls Cough
- Relieves Chest Congestion
- Thins & Loosens Mucus

FAST, EFFECTIVEcough relief

DMMAX

For Ages 12 & Over

4 FL OZ (118 mL)

Principal Display Panel – Robitussin Maximum Strength Nighttime Cough DM

ADULT

Robitussin

MAXIMUM STRENGTH

Nighttime Cough DM

DEXTROMETHORPHAN HBr (Cough Suppressant)

DOXYLAMINE SUCCINATE (Antihistamine)

- Controls Cough
- Relieves Runny Nose & Sneezing

FAST, EFFECTIVE cough relief

DMNIGHTTIME MAX

For Ages 12 & Over

4 FL OZ (118 mL)

Principal Display Panel – Robitussin Maximum Strength Day/Night Value Pack

DAY&NIGHT VALUE PACK

ADULT

Robitussin

MAXIMUM STRENGTH

COUGH+CHEST CONGESTION DM

DEXTROMETHORPHAN HBr (Cough Suppressant)

GUAIFENESIN (Expectorant)

- Controls Cough
- Relives Chest Congestion
- Thins & Loosens Mucus

FAST, EFFECTIVEcough relief

DMMAX

For Ages 12 & Over

4 FL OZ (118 mL)

MAXIMUM STRENGTH

Nighttime Cough DM

DEXTROMETHORPHAN HBr (Cough Suppressant)

DOXYLAMINE SUCCINATE (Antihistamine)

- Controls Cough
- Relieves Runny Nose & Sneezing

FAST, EFFECTIVEcough relief

DMNIGHTTIME MAX

For Ages 12 & Over

4 FL OZ (118 mL)